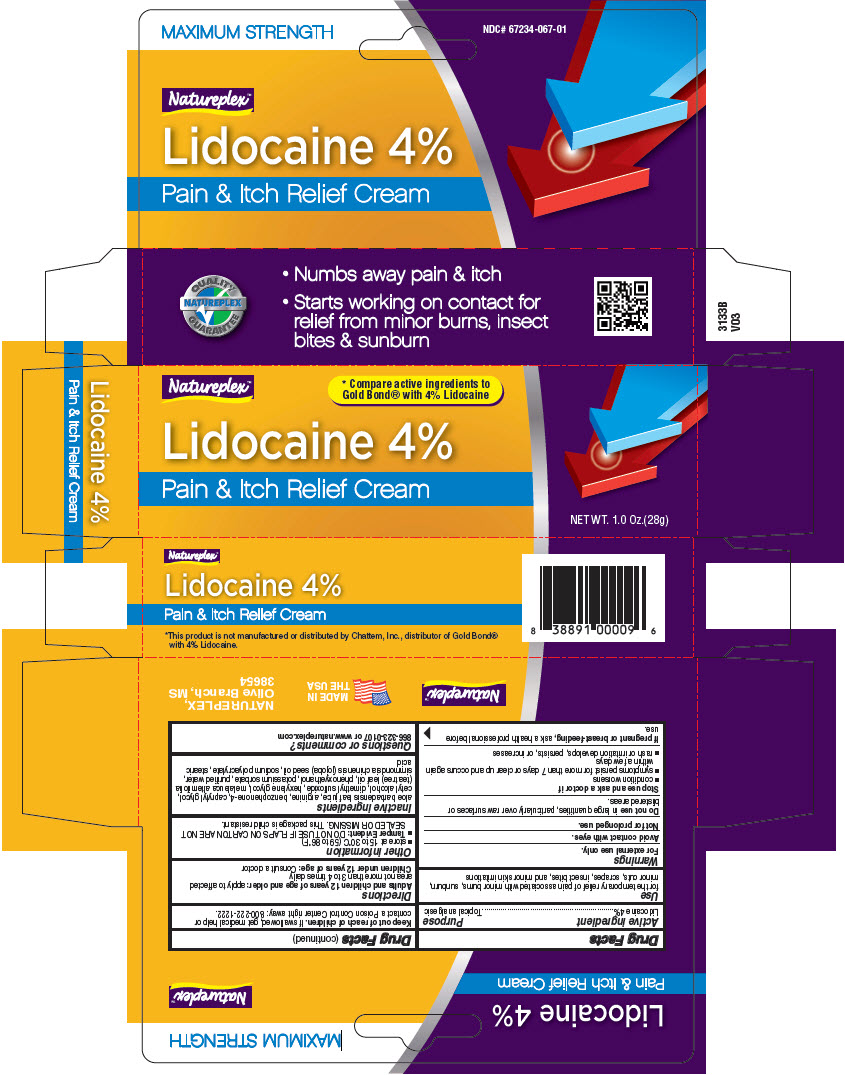 DRUG LABEL: Natureplex Lidocaine 4%
NDC: 67234-067 | Form: CREAM
Manufacturer: Natureplex LLC
Category: otc | Type: HUMAN OTC DRUG LABEL
Date: 20210511

ACTIVE INGREDIENTS: Lidocaine 0.04 g/28 g
INACTIVE INGREDIENTS: Aloe Vera Leaf; SULISOBENZONE; CAPRYLYL GLYCOL; Cetyl Alcohol; Dimethyl Sulfoxide; Hexylene Glycol; TEA TREE OIL; Phenoxyethanol; Potassium Sorbate; WATER; SIMMONDSIA CHINENSIS SEED; SODIUM POLYACRYLATE (8000 MW); Stearic Acid; Arginine

Natureplex™ Lidocaine 4%
Topical

Drug Facts

Active ingredient

Lidocaine 4%

Purpose

Topical analgesic

Use

for the temporary relief of pain associated with minor burns, sunburn, minor cuts, scrapes, insect bites, and minor skin irritations

Warnings

For external use only.

Avoid contact with eyes.

Not for prolonged use.

Do not use in large quantities, particularly over raw surfaces or blistered areas.

Stop use and ask a doctor if

- condition worsens
- symptoms persist for more than 7 days or clear up and occurs again within a few days
- rash or irritation develops, persists, or increases

PREGNANCY OR BREAST FEEDING

If pregnant or breast-feeding, ask a health professional before use.

Keep out of reach of children. If swallowed, get medical help or contact a Poison Control Center right away: 800-222-1222.

Directions

Adults and children 2 years of age and older: apply to affected area not more than 3 to 4 times daily

Children under 2 years of age: Consult a doctor

Other information

- store at 15 to 30°C (59 to 86°F)
- Tamper Evident: DO NOT USE IF SEAL ON TUBE IS PUNCTURED OR MISSING.

Inactive ingredients

aloe barbadensis leaf juice, arginine, benzophenone-4, caprylyl glycol, cetyl alcohol, dimethyl sulfoxide, hexylene glycol, melaleuca alternifolia (tea tree) leaf oil, phenoxyethanol, potassium sorbate, purified water, simmondsia chinensis (jojoba) seed oil, sodium polyacrylate, stearic acid

Questions or comments?

866-323-0107 or www.natureplex.com

PRINCIPAL DISPLAY PANEL - 28 g Tube Carton

Natureplex™

* Compare active ingredients to
Gold Bond® with 4% Lidocaine

Lidocaine 4%

Pain & Itch Relief Cream

NET WT. 1.0 Oz.(28g)